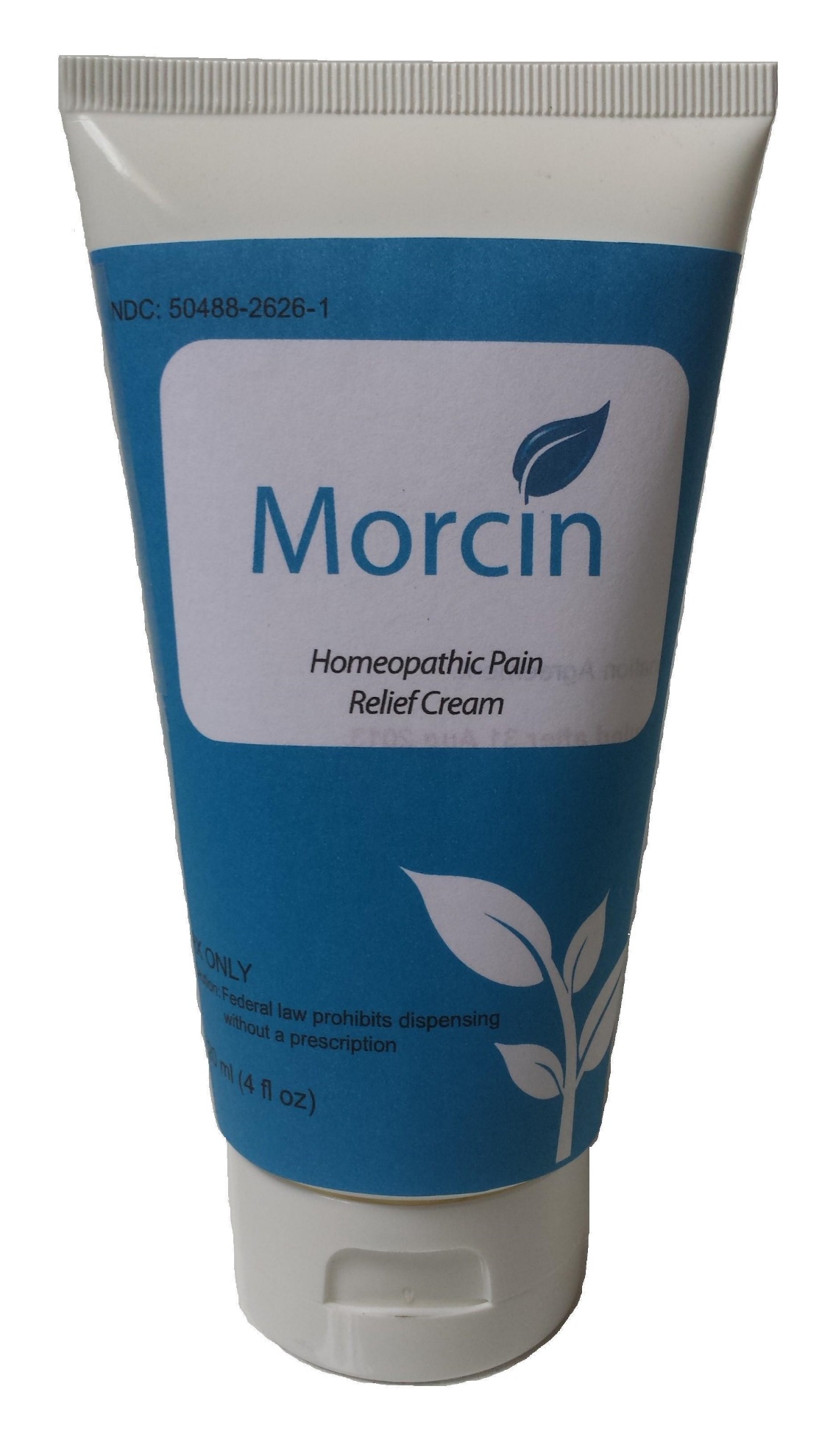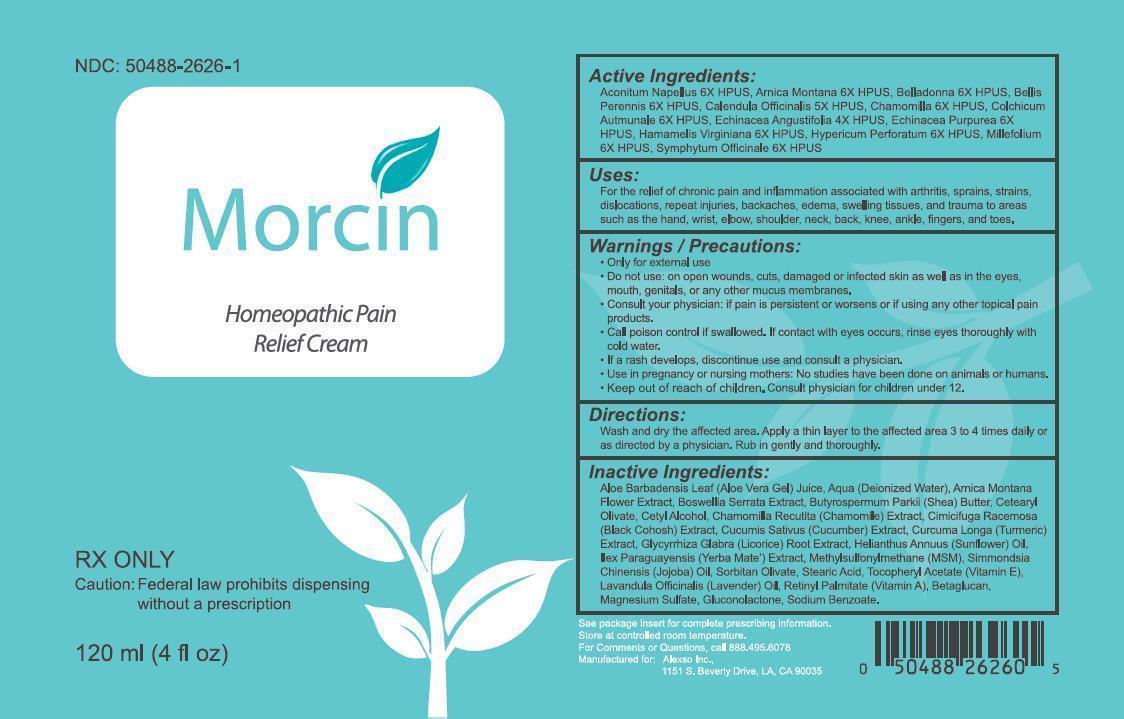 DRUG LABEL: Morcin
NDC: 50488-2626 | Form: CREAM
Manufacturer: Alexso, Inc
Category: homeopathic | Type: HUMAN PRESCRIPTION DRUG LABEL
Date: 20190211

ACTIVE INGREDIENTS: ACONITUM NAPELLUS 6 [hp_X]/120 mL; ARNICA MONTANA 6 [hp_X]/120 mL; BELLADONNA LEAF 6 [hp_X]/120 mL; BELLIS PERENNIS 6 [hp_X]/120 mL; CALENDULA OFFICINALIS FLOWER 5 [hp_X]/120 mL; MATRICARIA RECUTITA 6 [hp_X]/120 mL; ECHINACEA ANGUSTIFOLIA 4 [hp_X]/120 mL; COLCHICUM AUTUMNALE FLOWER 6 [hp_X]/120 mL; HAMAMELIS VIRGINIANA WHOLE 6 [hp_X]/120 mL; ECHINACEA PURPUREA 6 [hp_X]/120 mL; HYPERICUM PERFORATUM 6 [hp_X]/120 mL; ACHILLEA MILLEFOLIUM 6 [hp_X]/120 mL
INACTIVE INGREDIENTS: SYMPHYTUM OFFICINALE WHOLE 6 [hp_X]/120 mL; ALOE VERA WHOLE; WATER; ARNICA MONTANA FLOWER; BOSWELLIA SERRATA WHOLE; SHEA BUTTER; CETEARYL OLIVATE; CETYL ALCOHOL; CHAMOMILE; BLACK COHOSH; CUCUMBER; TURMERIC; LICORICE; SUNFLOWER OIL; ILEX PARAGUARIENSIS WHOLE; DIMETHYL SULFONE; JOJOBA OIL; SORBITAN OLIVATE; STEARIC ACID; .ALPHA.-TOCOPHEROL ACETATE; LAVENDER OIL; VITAMIN A; CURDLAN; MAGNESIUM SULFATE, UNSPECIFIED FORM; GLUCONOLACTONE; SODIUM BENZOATE

Morcin

WARNINGS AND PRECAUTIONS

Only for external use

Do not use on open wounds, cuts, damaged or infected skin as well as in the eyes, mouth, genitals or any other mucus membranes.

Consult your physician: if pain is persistent or worsens or if using any other topical pain products.

Call poison control if swallowed. If contact with eyes occurs, rinse eyes thoroughly with cold water.

If a rash develops discontinue use and consult a physician.

Use in pregnancy or nursing mother: No studies have been done on animals or humans.

Keep out of reach of children. Consult physician for children under 12.